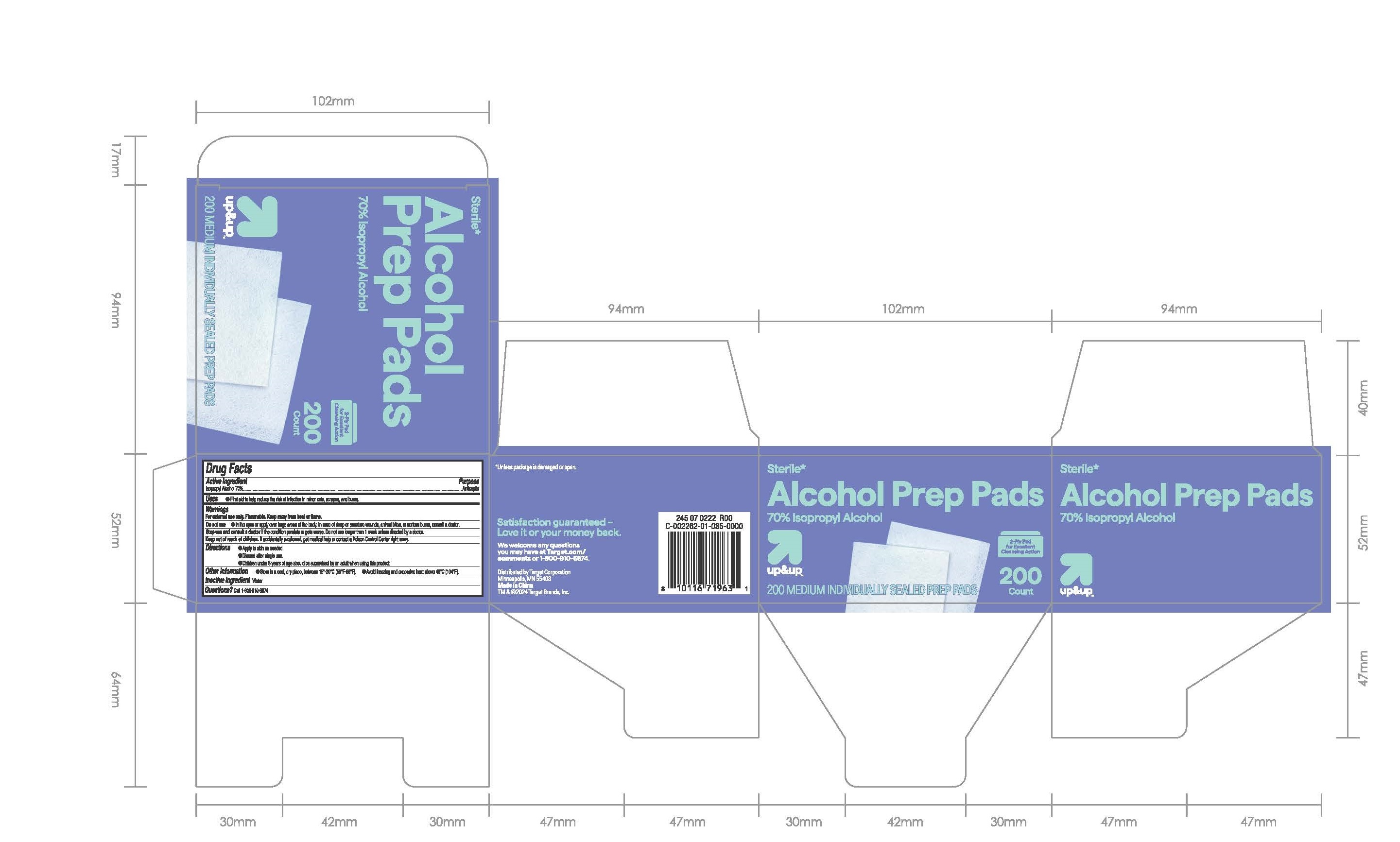 DRUG LABEL: Alcohol Prep Pads
NDC: 78691-026 | Form: SWAB
Manufacturer: QUEST USA CORP
Category: otc | Type: HUMAN OTC DRUG LABEL
Date: 20241210

ACTIVE INGREDIENTS: ISOPROPYL ALCOHOL 0.26 g/1 g
INACTIVE INGREDIENTS: WATER

up&up Alcohol Prep Pads

Active ingredient

Isopropyl Alcohol 70%

Purpose

Antiseptic

Uses

First aid to help reduce the risk of infection in minor cuts, scrapes, and burns.

Warnings

For external use only. Flammable. Keep away from heat or flame.

Stop use and ask a doctor

if the condition persists or gets worse. Do not use longer than 1 week unless directed by a doctor.

Do not use

- in the eyes or apply over large areas of the body. In case of deep or puncture wounds, animal bites, or serious bums, consult a doctor.

Keep out of reach of children.If accidentally swallowed, get medical help or contact a Poison Control Center right away.

Directions

- Apply to skin as needed.
- Discard after single use.
- Children under 6 years of age should be supervised by an adult when using this product.

Other information

- Store in a cool, dry place, between 15°-30°C(59°F-86°F).
- Avoid freezing and excessive heat above 40°C(104°F).

Inactive ingredients

Water

Questions?

Call 1-800-910-6874